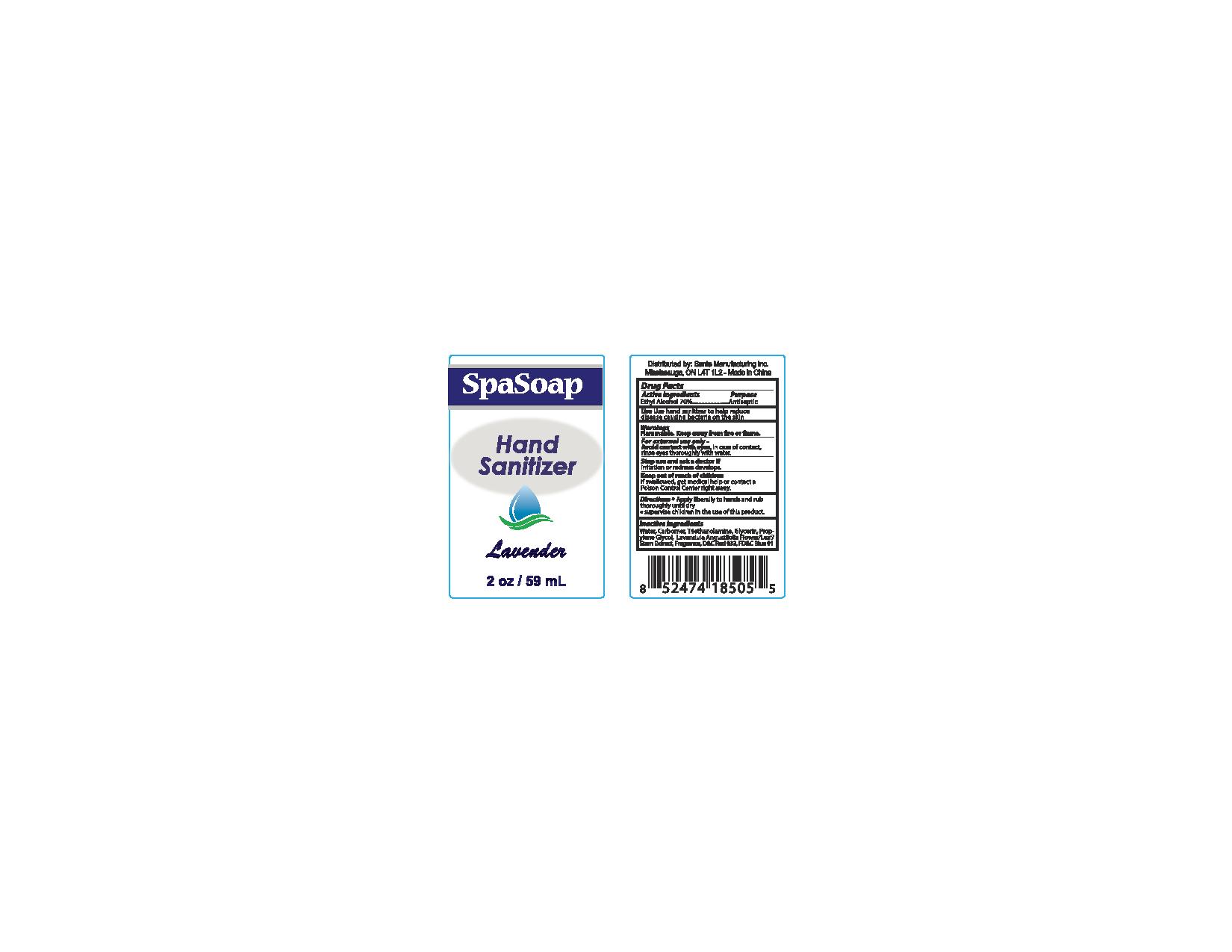 DRUG LABEL: Lavender
NDC: 71020-012 | Form: LIQUID
Manufacturer: Sante Manufacturing Inc
Category: otc | Type: HUMAN OTC DRUG LABEL
Date: 20170311

ACTIVE INGREDIENTS: ALCOHOL 700 mL/1000 mL
INACTIVE INGREDIENTS: CARBOMER 940; GLYCERIN; LAVANDULA ANGUSTIFOLIA FLOWER; TRIETHANOLAMINE LAURYL SULFATE; WATER; FD&C BLUE NO. 1; D&C RED NO. 33

Active Ingredients - Ethyl Alcohol 70%

Purpose - Antiseptic

Use

Use hand sanitizer to help reduce disease causing bacteria on the skin

Warnings

Flammable. Keep away from fire or flame

OTHER SAFETY INFORMATION

For external use only -

WHEN USING

Avoid contact with eyes. In case of contact, rinse eyes thoroughly with water

Stop use and ask a doctor if irritation or redness develops

Keep out of reach of children

If swallowed, get medical help or contact a Poison Control Center right away

Directions

- apply liberally to hands and rub thoroughly until dry
- supervise children in teh use of this product

INACTIVE INGREDIENT

Water, Carbomer, Triethanolamine, Glycerin, Propylene Glycol, Lavandula Angustifolia Flower / Leaf / Steam Extract, Fragrance, D&C Red#33, FD&C Blue # 1

PACKAGE LABEL

SpaSoap

Hand Sanitizer

Lavender

2oz / 59ml